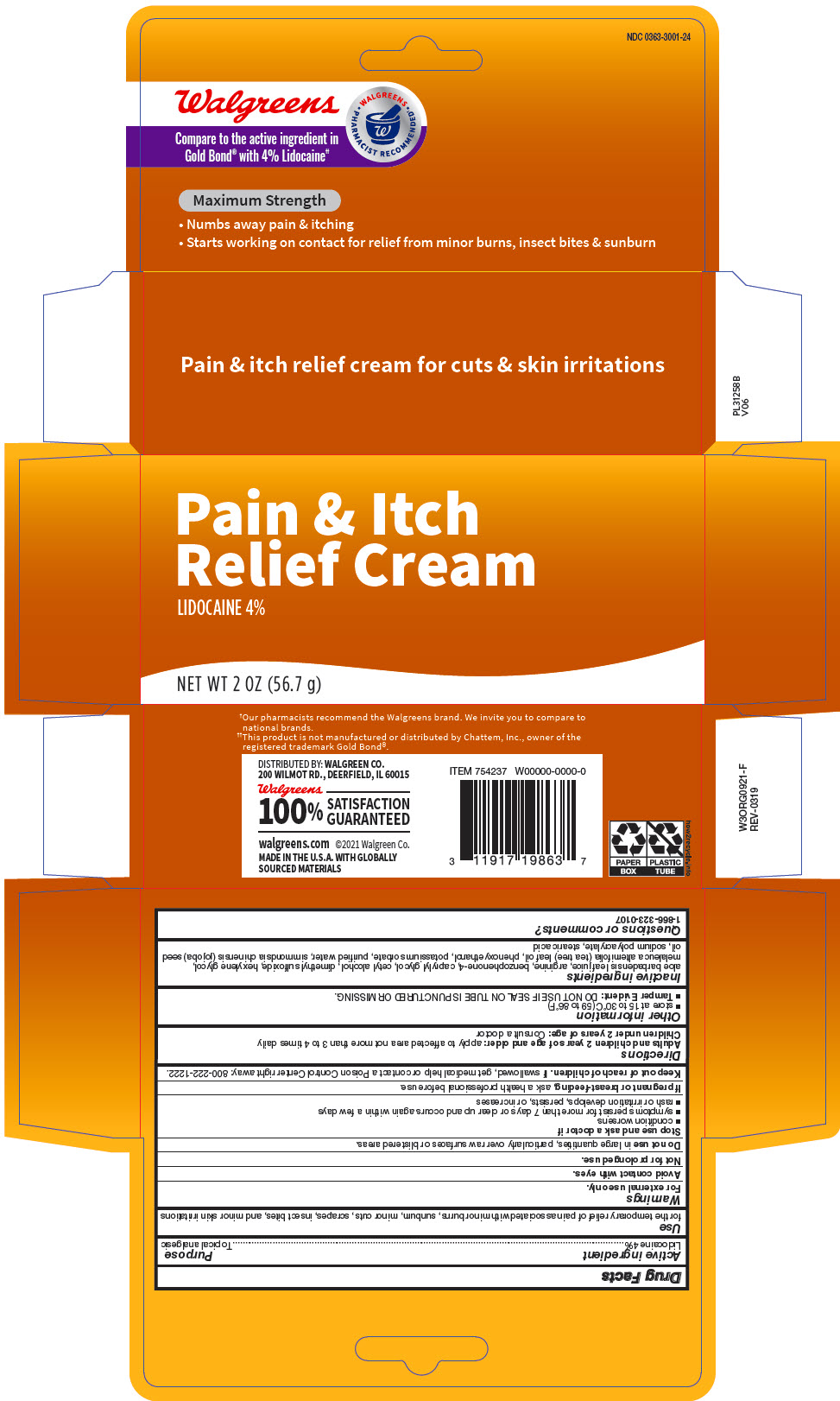 DRUG LABEL: Pain and Itch Relief 
NDC: 0363-3001 | Form: CREAM
Manufacturer: Walgreens
Category: otc | Type: HUMAN OTC DRUG LABEL
Date: 20251209

ACTIVE INGREDIENTS: Lidocaine 0.04 g/40 g
INACTIVE INGREDIENTS: aloe vera leaf; arginine; sulisobenzone; cetyl alcohol; dimethyl sulfoxide; melaleuca alternifolia whole; caprylyl glycol; potassium sorbate; water; hexylene glycol; jojoba oil; sodium polyacrylate (2500000 MW); stearic acid

Pain and Itch Relief Cream
4% Lidocaine

Drug Facts

Active ingredient

Lidocaine 4%

Purpose

Topical analgesic

Use

for the temporary relief of pain associated with minor burns, sunburn, minor cuts, scrapes, insect bites, and minor skin irritations

Warnings

For external use only.

Avoid contact with eyes.

Not for prolonged use.

Do not use in large quantities, particularly over raw surfaces or blistered areas.

Stop use and ask a doctor if

- condition worsens
- symptoms persist for more than 7 days or clear up and occurs again within a few days
- rash or irritation develops, persists, or increases

PREGNANCY OR BREAST FEEDING

If pregnant or breast-feeding, ask a health professional before use.

Keep out of reach of children. If swallowed, get medical help or contact a Poison Control Center right away: 800-222-1222.

Directions

Adults and children 2 years of age and older: apply to affected area not more than 3 to 4 times daily

Children under 2 years of age: Consult a doctor

Other information

- store at 15 to 30°C (59 to 86°F)
- Tamper Evident: DO NOT USE IF SEAL ON TUBE IS PUNCTURED OR MISSING.

Inactive ingredients

aloe barbadensis leaf juice, arginine, benzophenone-4, caprylyl glycol, cetyl alcohol, dimethyl sulfoxide, hexylene glycol, melaleuca alternifolia (tea tree) leaf oil, phenoxyethanol, potassium sorbate, purified water, simmondsia chinensis (jojoba) seed oil, sodium polyacrylate, stearic acid

Questions or comments?

1-866-323-0107

DISTRIBUTED BY: WALGREEN CO.
200 WILMOT RD., DEERFIELD, IL 60015

PRINCIPAL DISPLAY PANEL - 56.7 g Tube Carton

Pain & Itch
Relief Cream
LIDOCAINE 4%

NET WT 2 OZ (56.7 g)